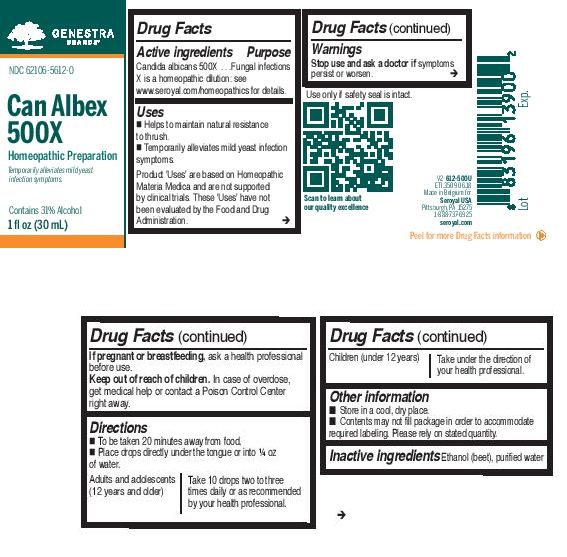 DRUG LABEL: Can Albex 500X
NDC: 62106-5612 | Form: LIQUID
Manufacturer: Seroyal USA
Category: homeopathic | Type: HUMAN OTC DRUG LABEL
Date: 20221109

ACTIVE INGREDIENTS: CANDIDA ALBICANS 500 [hp_X]/30 mL
INACTIVE INGREDIENTS: ALCOHOL; WATER

Can Albex 500X

Active ingredients

Candida albicans 500X

Uses

Helps promote and maintain natural resistance to thrush and alleviates symptoms associated with yeast infections.

Warnings
Stop use and ask a doctor if symptoms persist or worsen.

Keep out of reach of children.

In case of overdose, get medical help or contact a Poison Control Center right away.
If pregnant or breastfeeding, ask a health professional before use.

Stop use and ask a doctor if symptoms persist or worsen.

Keep out of reach of children.

OVERDOSAGE

In case of overdose, get medical help or contact a Poison Control Center right away.

PREGNANCY OR BREAST FEEDING

If pregnant or breastfeeding, ask a health professional before use.

Inactive ingredients

Ethanol (beet), purified water

Other information

Store in a cool, dry place.

Directions
To be taken 20 minutes away from food.
Place drops directly under the tongue or into ¼ oz of water.
Adults and adolescents (12 years and older)

Take 10 drops two to three times daily or as recommended by your healthcare practitioner.

Children (under 12 years)

Take under the direction of your healthcare practitioner.

Uses

Helps promote and maintain natural resistance to thrush and alleviates symptoms associated with yeast infections.

Directions
To be taken 20 minutes away from food.
Place drops directly under the tongue or into ¼ oz of water.
Adults and adolescents (12 years and older)

Take 10 drops two to three times daily or as recommended by your healthcare practitioner.

Children (under 12 years)

Take under the direction of your healthcare practitioner.

PACKAGE LABEL

Genestra Brands

NDC 62106-5612-0

Can Albex 500X

Homeopathic Preparation

Temporarily alleviates mild yeast
infection symptoms.

Contains 31% Alcohol
1 fl oz (30 mL)